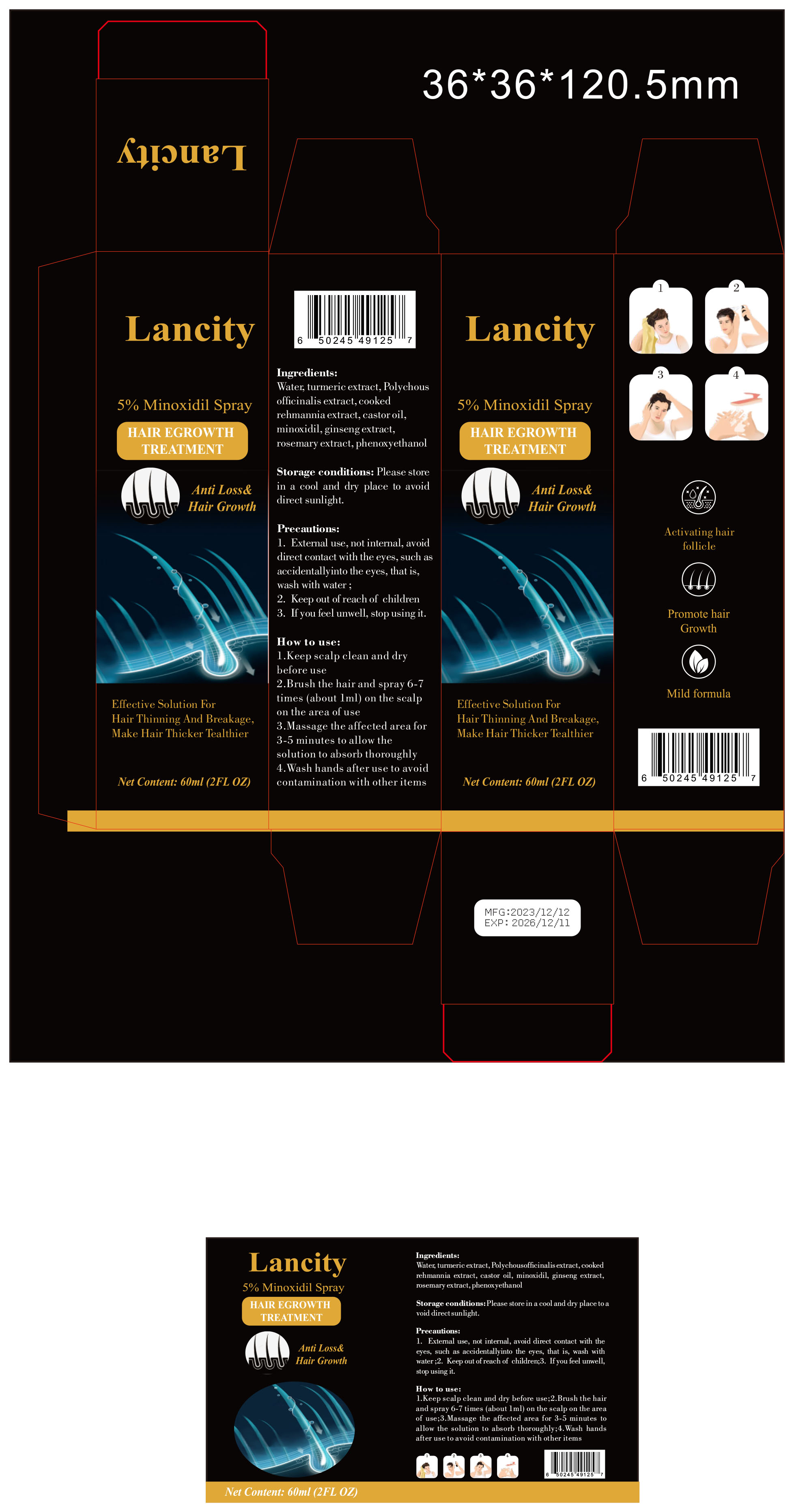 DRUG LABEL: 5% Minoxidil
NDC: 83889-101 | Form: OIL
Manufacturer: Shenzhen Lancity Information Technology Co., Ltd
Category: homeopathic | Type: HUMAN OTC DRUG LABEL
Date: 20241030

ACTIVE INGREDIENTS: MINOXIDIL 5 g/100 mL
INACTIVE INGREDIENTS: PHENOXYETHANOL; WATER; CASTOR OIL; TURMERIC; ASIAN GINSENG

5% Minoxidil Spray

ACTIVE INGREDIENT

Minoxidil 5%

PURPOSE

Effective Solution
ForHair Thinning And Breakage
Make Hair Thicker Tealthier

Keep out ofreach of children

INDICATIONS AND USAGE

1.Keep scalp clean and dry before use
2.Brush the hair and spray 6-7 times (about lml) on the scalp on the area of use
3.Massage the affected area for 3-5 minutes to allow the solution to absorb thoroughly
4.Wash hands after use to avoidcontamination with other items

WARNINGS

1.External use, not internal, avoiddirect contact with the eyes, such asaccidentallyinto the eyes, that is,wash with water ;
2. Keep out ofreach of children
3. If you feelunwell, stop using it.

DOSAGE AND ADMINISTRATION

Brush the hair and spray 6-7 times (about lml) on the scalpon the area of use

STORAGE AND HANDLING

Storage conditions: Please storein a cool and dry place to avoiddirect sunlight

INACTIVE INGREDIENT

Water
phenoxyethanol
turmeric extract
castor oil
ginseng extract